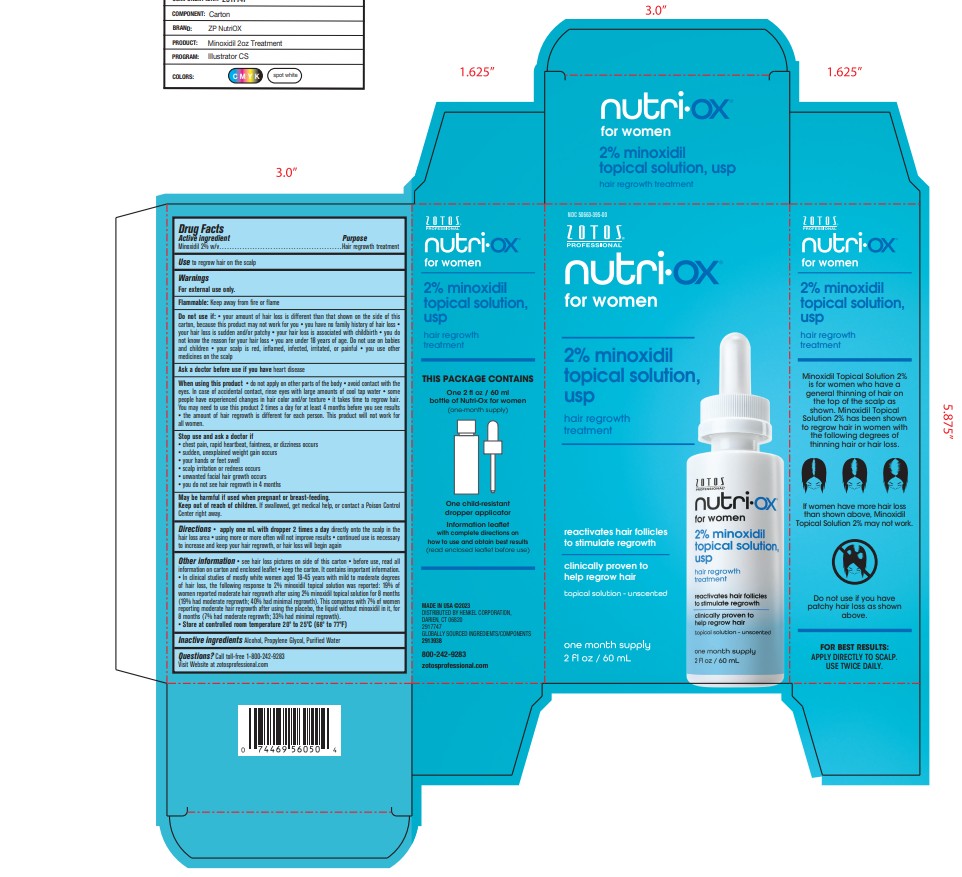 DRUG LABEL: Minoxidil Solution
NDC: 54340-211 | Form: SOLUTION/ DROPS
Manufacturer: Henkel Corporation
Category: otc | Type: HUMAN OTC DRUG LABEL
Date: 20251031

ACTIVE INGREDIENTS: MINOXIDIL 2 g/100 mL
INACTIVE INGREDIENTS: PROPYLENE GLYCOL 23 g/100 mL; WATER 18.5 g/100 mL; ALCOHOL 56.6 g/100 mL

Nutri-Ox Minoxidil

Active Ingredient

Minoxidil 2%

Purpose

To regrow hair on scalp

Uses

To regrow hair on the scalp.

Warnings

For external use only.

When using this product . do not apply on other parts of the body . avoid contact with the
eyes. In case of accidental contact, rinse eyes with large amounts of cool tap water . some
people have experienced changes in hair color and/or texture . it takes time to regrow hair.
You may need to use this product 2 times a day for at least 4 months before you see results
. the amount of hair regrowth is different for each person. This product will not work for
all women.

Stop use and ask doctor if

Stop use and ask a doctor if
. chest pain, rapid heartbeat, faintness, or dizziness occurs
. sudden, unexplained weight gain occurs
. your hands or feet swell
. scalp irritation or redness occurs
. unwanted facial hair growth occurs
. you do not see hair regrowth in 4 months

Keep out of reach of children.

If swallowed get medical help or contact a Poison Control Center right away.

Directions

Directions . apply one mL with dropper 2 times a day directly onto the scalp in the
hair loss area . using more or more often will not improve results . continued use is necessary
to increase and keep your hair regrowth, or hair loss will begin again

Inactive Ingredients

Alcohol, Propylene Glycol, Purified Water

Questions

Call toll-free 1-800-242-9283

Legal Entity

MADE IN USA C2023
DISTRIBUTED BY HENKEL CORPORATION,
DARIEN, CT 06820
2917747
GLOBALLY SOURCED INGREDIENTS/COMPONENTS
2913938

800-242-9283
zotosprofessional.com

Indications & Usage

Use to regrow hair on the salp.

Topical Liquid

Directions . apply one mL with dropper 2 times a day directly onto the scalp in the
hair loss area . using more or more often will not improve results . continued use is necessary
to increase and keep your hair regrowth, or hair loss will begin again